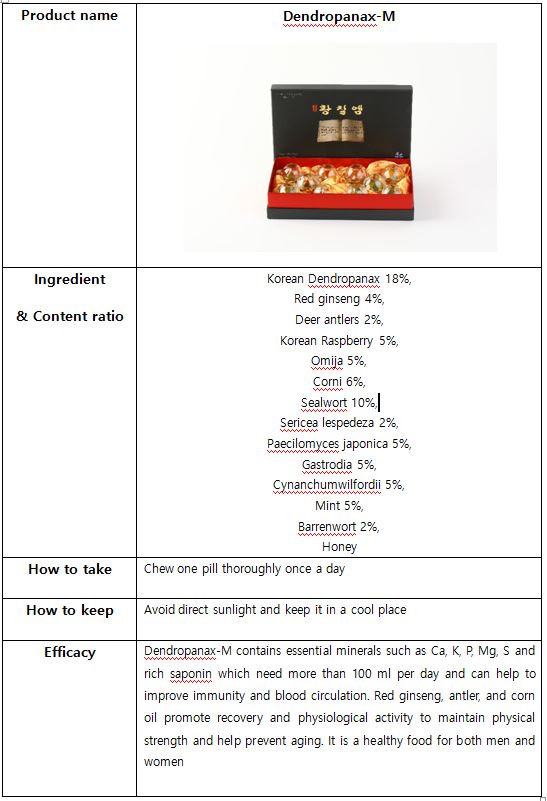 DRUG LABEL: DENDROPANAX M
NDC: 70694-0004 | Form: PILL
Manufacturer: Inc MBG
Category: otc | Type: HUMAN OTC DRUG LABEL
Date: 20190124

ACTIVE INGREDIENTS: PANAX GINSENG WHOLE 4 g/100 g
INACTIVE INGREDIENTS: RASPBERRY; HONEY

INDICATIONS AND USAGE

Chew one pill thoroughly once a day

Keep out of reach of children.

DOSAGE AND ADMINISTRATION

for oral use only

Do not use this product if the expiration date has passed

Hypersensitive reactions may occur for people with special needs and/or allergies. Please check the ingredients before intake

When opening the product and/or during intake, please be careful as you may get hurt from the packaging

Avoid direct sunlight and humid areas. Store and distribute in a cool area.

PURPOSE

Dendropanax-M contains essential minerals such as Ca, K, P, Mg, S and rich saponin which need more than 100 ml per day and can help to improve immunity and blood circulation. Red ginseng, antler, and corn oil promote recovery and physiological activity to maintain physical strength and help prevent aging. It is a healthy food for both men and women

INACTIVE INGREDIENT

Korean Dendropanax 18%,

Deer antlers 2%,

Korean Raspberry 5%,

Omija 5%,

Corni 6%,

Sealwort 10%,

Sericea lespedeza 2%,

Paecilomyces japonica 5%,

Gastrodia 5%,

Cynanchumwilfordii 5%,

Mint 5%,

Barrenwort 2%,

Honey

ACTIVE INGREDIENT

red ginseng